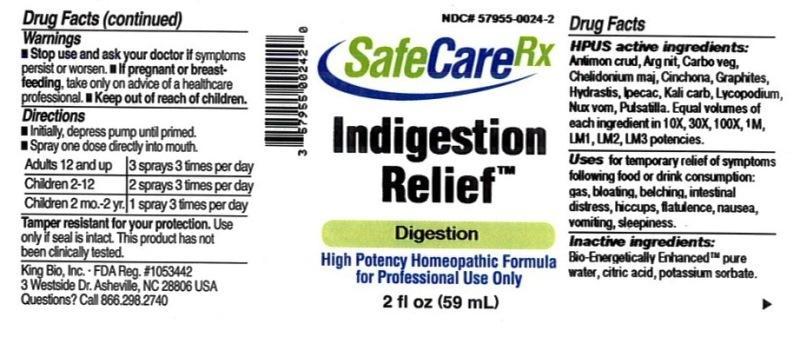 DRUG LABEL: Indigestion Relief
NDC: 57955-0024 | Form: LIQUID
Manufacturer: King Bio Inc.
Category: homeopathic | Type: HUMAN OTC DRUG LABEL
Date: 20150311

ACTIVE INGREDIENTS: ANTIMONY TRISULFIDE 10 [hp_X]/59 mL; SILVER NITRATE 10 [hp_X]/59 mL; ACTIVATED CHARCOAL 10 [hp_X]/59 mL; CHELIDONIUM MAJUS 10 [hp_X]/59 mL; CINCHONA OFFICINALIS BARK 10 [hp_X]/59 mL; GRAPHITE 10 [hp_X]/59 mL; GOLDENSEAL 10 [hp_X]/59 mL; IPECAC 10 [hp_X]/59 mL; POTASSIUM CARBONATE 10 [hp_X]/59 mL; LYCOPODIUM CLAVATUM SPORE 10 [hp_X]/59 mL; STRYCHNOS NUX-VOMICA SEED 10 [hp_X]/59 mL; PULSATILLA VULGARIS 10 [hp_X]/59 mL
INACTIVE INGREDIENTS: WATER; ANHYDROUS CITRIC ACID; POTASSIUM SORBATE

Indigestion Relief™

ACTIVE INGREDIENT

Drug Facts__________________________________________________________________________________________________________

HPUS active ingredients: Antimonium crudum, Argentum nitricum, Carbo vegetabilis, Chelidonium majus, Cinchona officinalis, Graphites, Hydrastis canadensis, Ipecacuanha, Kali carbonicum, Lycopodiumj clavatum, Nux vomica, Pulsatilla. Equal volumes of each ingredient in 10X, 30X, 100X, 1M, LM1, LM2, LM3 potencies.

INDICATIONS AND USAGE

Uses for temporary relief of symptoms following food or drink consumption: gas, bloating, belching, intestinal distress, hiccups, flatulence, nausea, vomiting, sleepiness.

Inactive Ingredients:

Bio-Energetically Enhanced™ pure water, citric acid and potassium sorbate.

Warnings

- Stop use and ask your doctor if symptoms persist or worsen.
- If pregnant or breast-feeding, take only on advice of a healthcare professional.

- Keep out of reach of children.

Directions

- Initially, depress pump until primed.
- Spray one dose directly into mouth.
- Adults 12 and up: 3 sprays 3 times per day
- Children 2-12: 2 sprays 3 times per day
- Children 2 mo-2yr: 1 spray 3 times per day

OTHER SAFETY INFORMATION

Tamper resistant for your protection. Use only if safety seal is intact.

PURPOSE

Uses for temporary relief of symptoms following food or drink consumption:

- gas
- bloating
- belching
- intestinal distress
- hiccups
- flatulence
- nausea
- vomiting
- sleepiness